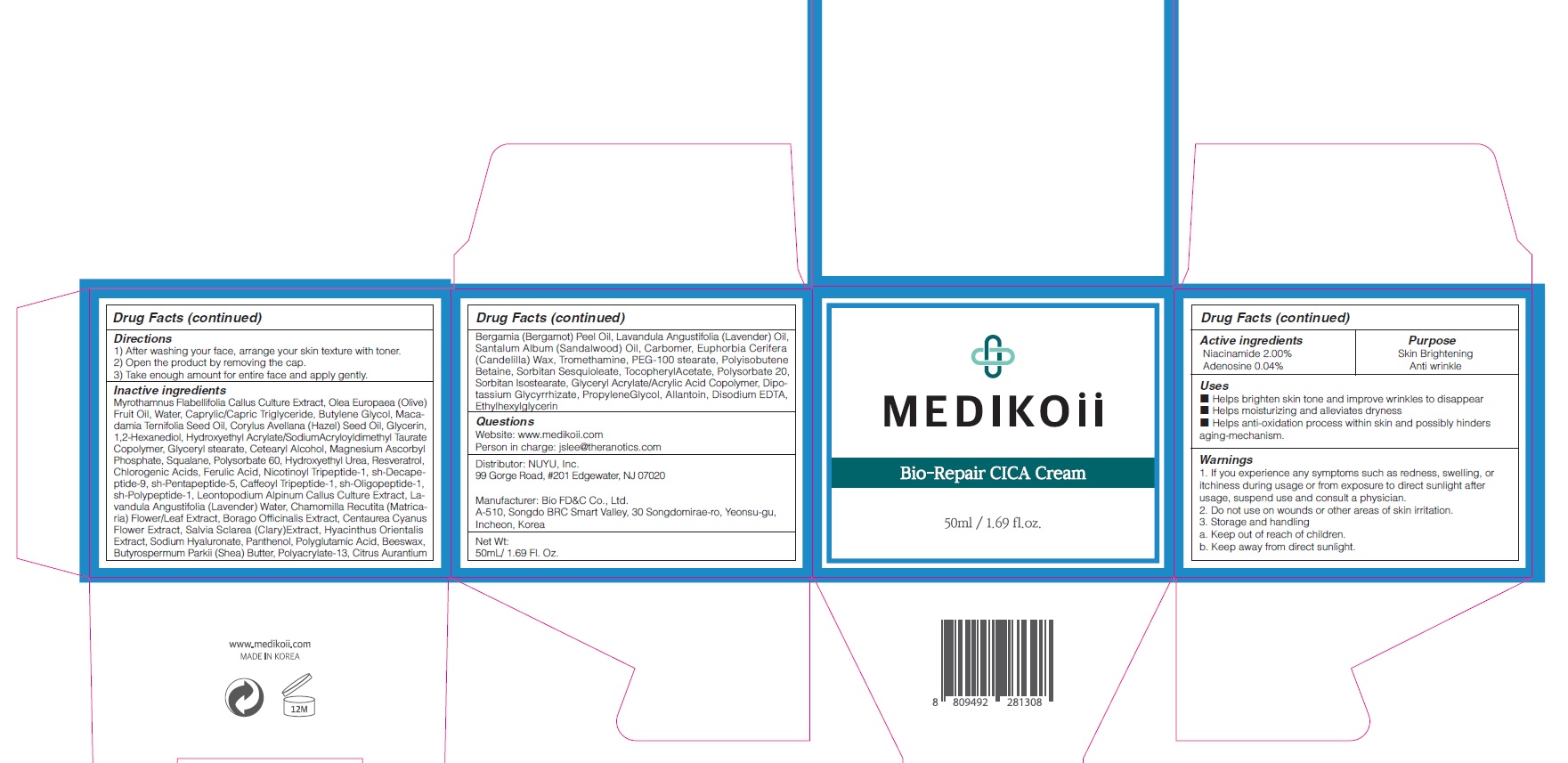 DRUG LABEL: MEDIKOii Bio Repair CICA
NDC: 72695-0013 | Form: CREAM
Manufacturer: THERANOTICS CO.,LTD.
Category: otc | Type: HUMAN OTC DRUG LABEL
Date: 20200529

ACTIVE INGREDIENTS: Niacinamide 2 g/100 mL; ADENOSINE 0.04 g/100 mL
INACTIVE INGREDIENTS: OLIVE OIL; Water

Drug Facts

ACTIVE INGREDIENTS

Niacinamide 2.00%
Adenosine 0.04%

INACTIVE INGREDIENTS

Myrothamnus Flabellifolia Callus Culture Extract, Olea Europaea (Olive) Fruit Oil, Water, Caprylic/Capric Triglyceride, Butylene Glycol, Macadamia Ternifolia Seed Oil, Corylus Avellana (Hazel) Seed Oil, Glycerin, 1,2-Hexanediol, Hydroxyethyl Acrylate/SodiumAcryloyldimethyl Taurate Copolymer, Glyceryl stearate, Cetearyl Alcohol, Magnesium Ascorbyl Phosphate, Squalane, Polysorbate 60, Hydroxyethyl Urea, Resveratrol, Chlorogenic Acids, Ferulic Acid, Nicotinoyl Tripeptide-1, sh-Decapeptide-9, sh-Pentapeptide-5, CaffeoylTripeptide-1, sh-Oligopeptide-1, sh-Polypeptide-1, Leontopodium Alpinum Callus Culture Extract, Lavandula Angustifolia (Lavender) Water, Chamomilla Recutita (Matricaria) Flower/Leaf Extract, Borago Officinalis Extract, Centaurea Cyanus Flower Extract, Salvia Sclarea (Clary)Extract, Hyacinthus Orientalis Extract, Sodium Hyaluronate, Panthenol, Polyglutamic Acid, Beeswax, Butyrospermum Parkii (Shea) Butter, Polyacrylate-13, Citrus Aurantium Bergamia (Bergamot) Peel Oil, Lavandula Angustifolia (Lavender) Oil, Santalum Album (Sandalwood) Oil, Carbomer, Euphorbia Cerifera (Candelilla) Wax, Tromethamine, PEG-100 stearate, Polyisobutene, Betaine, Sorbitan Sesquioleate, TocopherylAcetate, Polysorbate 20, Sorbitan Isostearate, Glyceryl Acrylate/Acrylic Acid Copolymer, Dipotassium Glycyrrhizate, PropyleneGlycol, Allantoin, Disodium EDTA, Ethylhexylglycerin

PURPOSE

Skin Brightening
Anti wrinkle

WARNINGS

1.If you experience any symptoms such as redness, swelling, or itchiness during usage or from exposure to direct sunlight after usage, suspend use and consult a physician.
2. Do not use on wounds or other areas of skin irritation.
3. Storage and handling
a. Keep out of reach of children.
b. Keep away from direct sunlight.

KEEP OUT OF REACH OF CHILDREN

Uses

■ Helps brighten skin tone and improve wrinkles to disappear
■ Helps moisturizing and alleviates dryness
■ Helps anti-oxidation process within skin and possibly hinders aging-mechanism.

Directions

1) After washing your face, arrange your skin texture with toner.
2) Open the product by removing the cap.
3) Take enough amount for entire face and apply gently.

QUESTIONS

Website: www.medikoii.com
Person in charge: jslee@theranotics.com